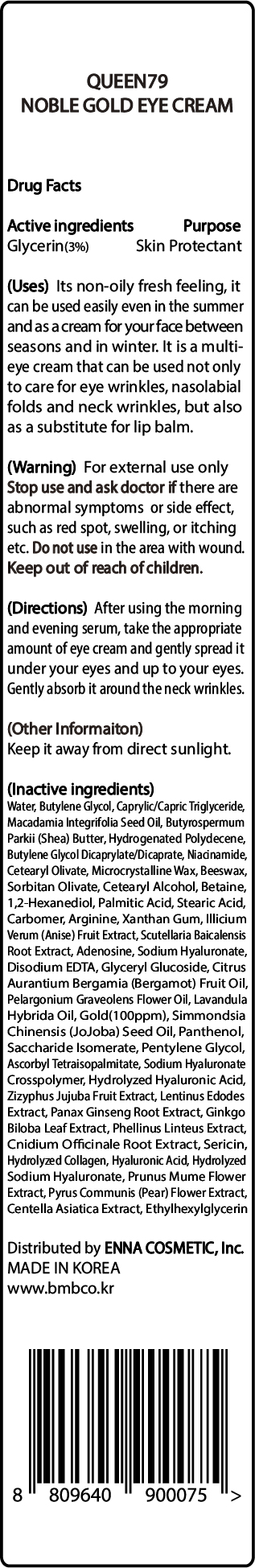 DRUG LABEL: QUEEN79 NOBLE GOLD EYECREAM
NDC: 81810-303 | Form: CREAM
Manufacturer: ENNA COSMETIC, Inc.
Category: otc | Type: HUMAN OTC DRUG LABEL
Date: 20230531

ACTIVE INGREDIENTS: GLYCERIN 3 mg/100 mL
INACTIVE INGREDIENTS: LAVANDIN OIL; EDETATE DISODIUM ANHYDROUS; PANTHENOL; SACCHARIDE ISOMERATE; CENTELLA ASIATICA; YELLOW WAX; ETHYLHEXYLGLYCERIN; SHEA BUTTER; BUTYLENE GLYCOL DICAPRYLATE/DICAPRATE; STAR ANISE FRUIT; CETOSTEARYL ALCOHOL; BETAINE; STEARIC ACID; ADENOSINE; PALMITIC ACID; LENTINULA EDODES MYCELIUM; JUJUBE FRUIT; ASIAN GINSENG; GINKGO; CNIDIUM OFFICINALE ROOT; ASCORBYL TETRAISOPALMITATE; SCUTELLARIA BAICALENSIS ROOT; WATER; CETEARYL OLIVATE; NIACINAMIDE; 1,2-HEXANEDIOL; XANTHAN GUM; GOLD; HYALURONATE SODIUM; HYALURONIC ACID; BERGAMOT OIL; JOJOBA OIL; PYRUS COMMUNIS FLOWER; MACADAMIA OIL; BUTYLENE GLYCOL; MEDIUM-CHAIN TRIGLYCERIDES; SORBITAN OLIVATE; SILK SERICIN; MICROCRYSTALLINE WAX; PENTYLENE GLYCOL; PRUNUS MUME FLOWER; ARGININE; PELARGONIUM GRAVEOLENS FLOWER OIL

81810-303 QUEEN79 NOBLE GOLD EYE CREAM

Active ingredients

Glycerin(3%)

Purpose

Skin Protectant

Uses

Its non-oily fresh feeling, it can be used easily even in the summer and as a cream for your face between seasons and in winter. It is a multi-eye cream that can be used not only to care for eye wrinkles, nasolabial folds and neck wrinkles, but also as a substitute for lip balm.

Warning

For external use only

Stop use and ask doctor if

there are abnormal symptoms or side effects, such as red spot, swelling, or itching etc.

Do not use

in the area with wound.

Keep out of reach of children

Directions

After using the morning and evening serum, take the appropriate amount of eye cream and gently spread it under your eyes and up to your eyes, Gently absorb it around the neck wrinkles.

Other Information

Keep it away from direct sunlight.

Inactive ingredients

WATER, BUTYLENE GLYCOL, CAPRYLIC/CAPRIC TRIGLYCERIDE, MACADAMIA INTEGRIFOLIA SEED OIL, BUTYROSPERMUM PARKII (SHEA BUTTER), HYDROGENATED POLYDECENE, BUTYLENE GLYCOL DICAPRYLATE/DICAPRATE, NIACINAMIDE, CETEARYL OLIVATE, MICROCRYSTALLINE WAX, BEESWAX, SORBITAN OLIVATE, CETEARYL ALCOHOL, BETAINE, 1,2-HEXANEDIOL, PALMITIC ACID, STEARIC ACID, CARBOMER, ARGININE, XANTHAN GUM, ILLICIUM VERUM (ANISE) FRUIT EXTRACT, SCUTELLARIA BAICALENSIS ROOT EXTRACT, ADENOSINE, SODIUM HYALURONATE, DISODIUM EDTA, GLYCERYL GLUCOSIDE, CITRUS AURANTIUM BERGAMIA (BERGAMOT) FRUIT OIL, PELARGONIUM GRAVEOLENS FLOWER OIL, LAVANDULA HYBRIDA OIL, GOLD(100ppm), SIMMONDSIA CHINENSIS (JOJOBA) SEED OIL, PANTHENOL, SACCHARIDE ISOMERATE, PENTYLENE GLYCOL, ASCORBYL TETRAISOPALMITATE, SODIUM HYALURONATE CROSSPOLYMER, HYDROLYZED HYALURONIC ACID, ZIZYPHUS JUJUBA FRUIT EXTRACT, LENTINUS EDODES EXTRACT, PANAX GINSENG ROOT EXTRACT, GINKGO BILOBA LEAF EXTRACT, PHELLINUS LINTEUS EXTRACT, CNIDIUM OFFICINALE ROOT EXTRACT, SERICIN, HYDROLYZED COLLAGEN, HYALURONIC ACID, HYDROLYZED SODIUM HYALURONATE, PRUNUS MUME FLOWER EXTRACT, PYRUS COMMUNIS (PEAR) FLOWER EXTRACT, CENTELLA ASIATICA EXTRACT, ETHYLHEXYLGLYCERIN